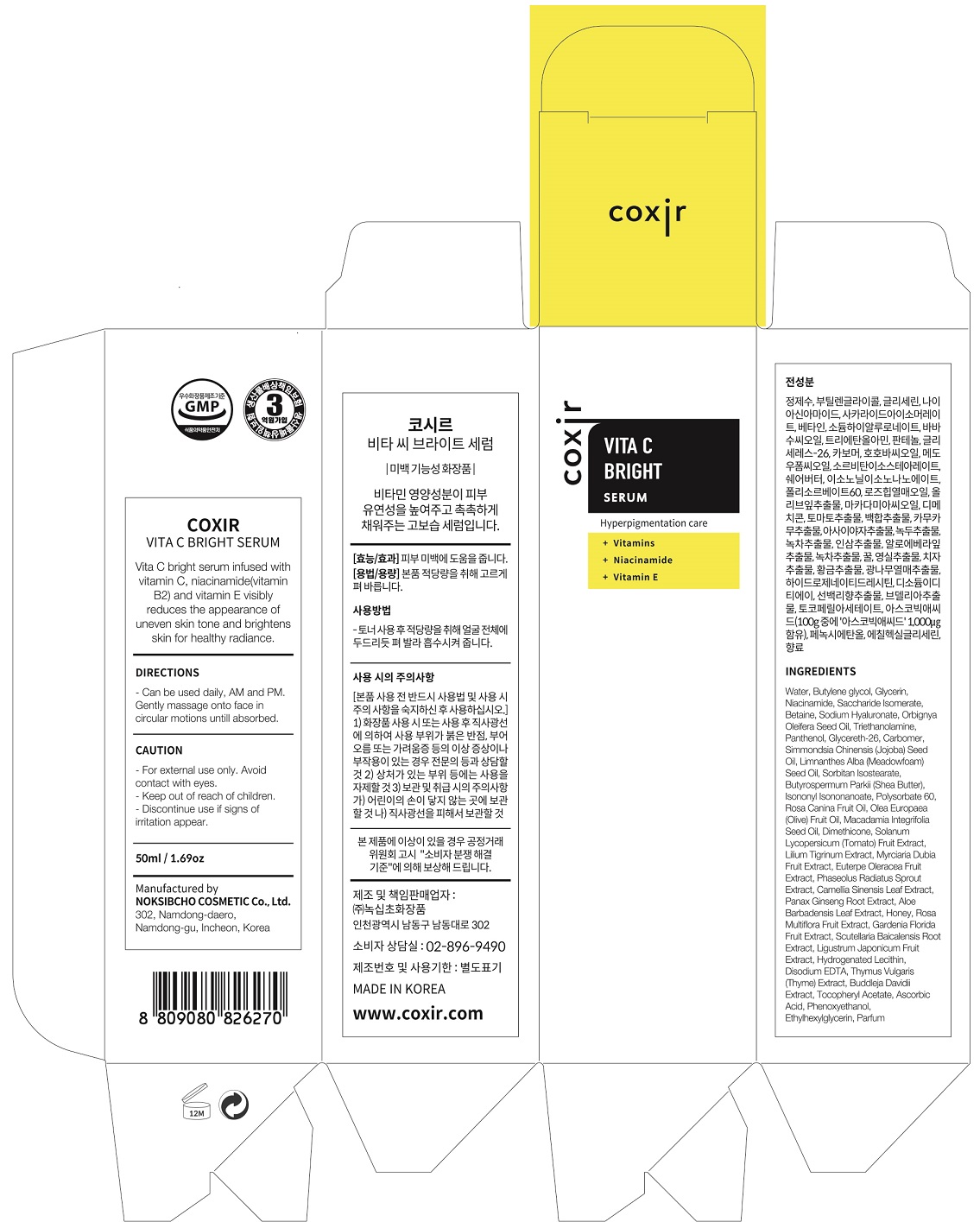 DRUG LABEL: Vita C Bright Serum
NDC: 73590-0017 | Form: LIQUID
Manufacturer: NOKSIBCHO cosmetic Co., Ltd.
Category: otc | Type: HUMAN OTC DRUG LABEL
Date: 20200314

ACTIVE INGREDIENTS: NIACINAMIDE 2 g/100 mL
INACTIVE INGREDIENTS: WATER; BUTYLENE GLYCOL

Drug Facts

ACTIVE INGREDIENT

niacinamide, vitamins, vitamin E

INACTIVE INGREDIENT

Water
Butylene glycol
Glycerin
Niacinamide
Saccharide Isomerate
Betaine
Sodium Hyaluronate
Orbignya Oleifera Seed Oil
Triethanolamine
Panthenol
Glycereth-26
Carbomer
Simmondsia Chinensis (Jojoba) Seed Oil
Limnanthes Alba (Meadowfoam) Seed Oil
Sorbitan Isostearate
Butyrospermum Parkii (Shea Butter)
Isononyl Isononanoate
Polysorbate 60
Rosa Canina Fruit Oil
Olea Europaea (Olive) Fruit Oil
Macadamia Integrifolia Seed Oil
Dimethicone
Solanum Lycopersicum (Tomato) Fruit Extract
Lilium Tigrinum Extract
Myrciaria Dubia Fruit Extract
Euterpe Oleracea Fruit Extract
Phaseolus Radiatus Sprout Extract
Camellia Sinensis Leaf Extract
Panax Ginseng Root Extract
Aloe Barbadensis Leaf Extract
Camellia Sinensis Leaf Extract
Honey
Rosa Multiflora Fruit Extract
Gardenia Florida Fruit Extract
Scutellaria Baicalensis Root Extract
Ligustrum Japonicum Fruit Extract
Carbomer
Hydrogenated Lecithin
Disodium EDTA
Thymus Vulgaris (Thyme) Extract
Buddleja Davidii Extract
Tocopheryl Acetate
Ascorbic Acid
Phenoxyethanol
Ethylhexylglycerin
Parfum

PURPOSE

hyperpigmentation care

keep out of reach of the children

INDICATIONS AND USAGE

apply proper amount and gently massage

WARNINGS

For external use only
When using this product

■ if the following symptoms occurs after use, stop use and consult with a skin specialist

red specks, swelling, itching

■ don’t use on the part where there is injury, eczema, or dermatitis

Keep out of reach of children

■ if swallowed, get medical help or contact a person control center immediately

DOSAGE AND ADMINISTRATION

for external use only